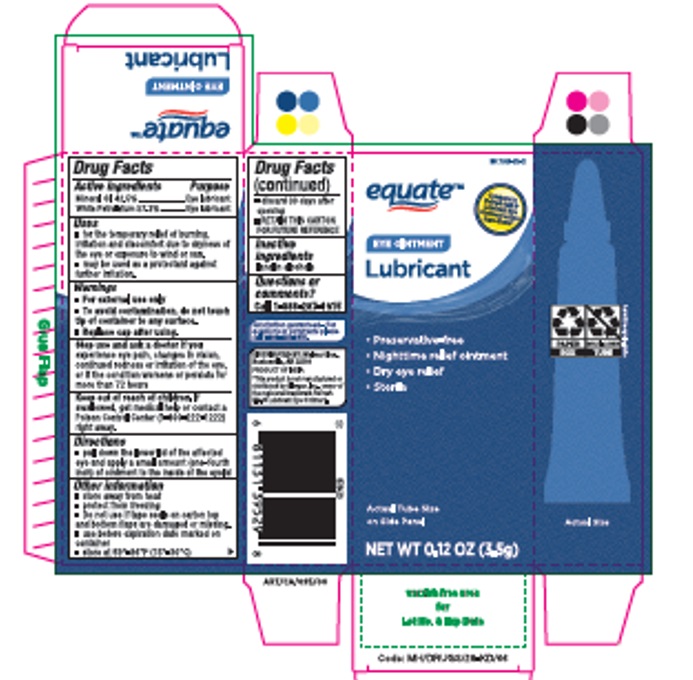 DRUG LABEL: EQUATE EYE LUBRICANT
NDC: 79903-026 | Form: OINTMENT
Manufacturer: WALMART STORES INC
Category: otc | Type: HUMAN OTC DRUG LABEL
Date: 20221120

ACTIVE INGREDIENTS: MINERAL OIL 425 mg/1 g; PETROLATUM 573 mg/1 g
INACTIVE INGREDIENTS: LANOLIN ALCOHOLS

Lubricant Eye Ointment

Active ingredients

Mineral Oil 42.5%

White Petrolatum 57.3%

Purpose

Eye lubricant

Uses

- For the temporary relief of burning, irritation, and discomfort due to dryness of the eye or exposure to wind or sun.
- May be used as a protectant against further irritation.

Warnings

- For external use only.
- To avoid contamination, do not touch tip of container to any surface.
- Replace cap after using.

Stop use and ask a doctor if you

experience eye pain, changes in vision, continued redness or irritation of the eye, or if the condition worsens or persists for more than 72 hours.

Keep out of reach of children.

If swallowed, get medical help or contact a Poison Control Center right away.

Directions

Pull down the lower lid of the affected eye and apply a small amount (one-fourth inch) of ointment to the inside of the eyelid.

Other information

- Store away from heat.
- Protect from freezing.
- Use only if imprinted tape seals on top and bottom flaps are intact and clearly legible.
- Use before expiration date marked on container.
- Store at 59°-86°F (15°-30°C).
- RETAIN THIS CARTON FOR FUTURE REFERENCE.

Inactive ingredients

Lanolin alcohols.